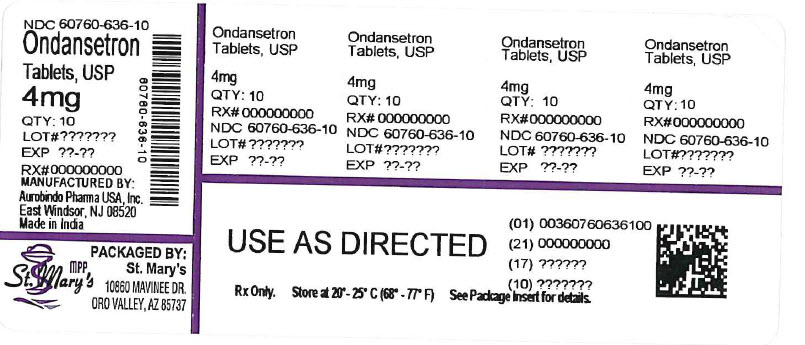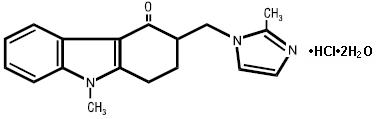 DRUG LABEL: Ondansetron Hydrochloride
NDC: 60760-636 | Form: TABLET, FILM COATED
Manufacturer: St. Mary's Medical Park Pharmacy
Category: prescription | Type: HUMAN PRESCRIPTION DRUG LABEL
Date: 20260227

ACTIVE INGREDIENTS: ONDANSETRON HYDROCHLORIDE 4 mg/1 1
INACTIVE INGREDIENTS: ANHYDROUS LACTOSE; CELLULOSE, MICROCRYSTALLINE; STARCH, CORN; MAGNESIUM STEARATE; TRIACETIN; TITANIUM DIOXIDE; HYPROMELLOSE 2910 (6 MPA.S)

HIGHLIGHTS OF PRESCRIBING INFORMATION

These highlights do not include all the information needed to use ONDANSETRON TABLETS safely and effectively. See full prescribing information for ONDANSETRON TABLETS.
ONDANSETRON tablets, for oral use
Initial U.S. Approval: 1991

1 INDICATIONS AND USAGE

Ondansetron tablets are a 5-HT3 receptor antagonist indicated for the prevention of:

- nausea and vomiting associated with highly emetogenic cancer chemotherapy, including cisplatin greater than or equal to 50 mg/m^2. (1)
- nausea and vomiting associated with initial and repeat courses of moderately emetogenic cancer chemotherapy. (1)
- nausea and vomiting associated with radiotherapy in patients receiving either total body irradiation, single high-dose fraction to the abdomen, or daily fractions to the abdomen. (1)
- postoperative nausea and/or vomiting. (1)

2 DOSAGE AND ADMINISTRATION

- See full prescribing information for the recommended dosage in adults and pediatrics. (2)
- Patients with severe hepatic impairment: do not exceed a total daily dose of 8 mg. (2.2, 8.6)

3 DOSAGE FORMS AND STRENGTHS

- Tablets: 4 mg, 8 mg, and 24 mg (3)

4 CONTRAINDICATIONS

- Patients known to have hypersensitivity (e.g., anaphylaxis) to ondansetron or any components of the formulation. (4)
- Concomitant use of apomorphine. (4)

5 WARNINGS AND PRECAUTIONS

- Hypersensitivity reactions including anaphylaxis and bronchospasm: Discontinue ondansetron if suspected. Monitor and treat promptly per standard of care until signs and symptoms resolve (5.1)
- QT interval prolongation and Torsade de Pointes: Avoid in patients with congenital long QT syndrome; monitor with electrocardiograms (ECGs) if concomitant electrolyte abnormalities, cardiac failure or arrhythmias, or use of other QT prolonging drugs. (5.2)
- Serotonin syndrome: Reported with 5-HT3 receptor antagonists alone but particularly with concomitant use of serotonergic drugs. If such symptoms occur, discontinue ondansetron and initiate supportive treatment. If concomitant use of ondansetron with other serotonergic drugs is clinically warranted, patients should be made aware of a potential increased risk for serotonin syndrome. (5.3)
- Masking of progressive ileus and/or gastric distention following abdominal surgery or chemotherapy-induced nausea and vomiting: Monitor for decreased bowel activity, particularly in patients with risk factors for gastrointestinal obstruction. (5.4)

6 ADVERSE REACTIONS

The most common adverse reactions in adults for the:

- prevention of chemotherapy-induced (greater than or equal to 5%) are: headache, malaise/fatigue, constipation, diarrhea. (6.1)
- prevention of radiation-induced nausea and vomiting (greater than or equal to 2%) are: headache, constipation, and diarrhea. (6.1)
- prevention of postoperative nausea and vomiting (greater than or equal to 9%) are: headache and hypoxia. (6.1)

To report SUSPECTED ADVERSE REACTIONS, contact Aurobindo Pharma USA, Inc. at 1-866-850-2876 or FDA at 1-800-FDA-1088 or www.fda.gov/medwatch.

FULL PRESCRIBING INFORMATION

1 INDICATIONS AND USAGE

Ondansetron tablets are indicated for the prevention of nausea and vomiting associated with:

- highly emetogenic cancer chemotherapy, including cisplatin greater than or equal to 50 mg/m^2.
- initial and repeat courses of moderately emetogenic cancer chemotherapy.
- radiotherapy in patients receiving either total body irradiation, single high-dose fraction to the abdomen, or daily fractions to the abdomen.

Ondansetron tablets are also indicated for the prevention of postoperative nausea and/or vomiting.

2 DOSAGE AND ADMINISTRATION

2.1 Dosage

The recommended dosage regimens for adult and pediatric patients are described in Table 1 and Table 2, respectively.
Corresponding doses of ondansetron tablets, ondansetron orally disintegrating tablets and ondansetron oral solution may be used interchangeably.

Table 1: Adult Recommended Dosage Regimen for Prevention of Nausea and Vomiting
Indication | Dosage Regimen
Highly Emetogenic Cancer Chemotherapy | A single 24 mg dose administered 30 minutes before the start of single-day highly emetogenic chemotherapy, including cisplatin greater than or equal to 50 mg/m^2
Moderately Emetogenic Cancer Chemotherapy | 8 mg administered 30 minutes before the start of chemotherapy, with a subsequent 8 mg dose 8 hours after the first dose. Then administer 8 mg twice a day (every 12 hours) for 1 to 2 days after completion of chemotherapy.
Radiotherapy | For total body irradiation: 8 mg administered 1 to 2 hours before each fraction of radiotherapy each day. For single high-dose fraction radiotherapy to the abdomen: 8 mg administered 1 to 2 hours before radiotherapy, with subsequent 8 mg doses every 8 hours after the first dose for 1 to 2 days after completion of radiotherapy. For daily fractionated radiotherapy to the abdomen: 8 mg administered 1 to 2 hours before radiotherapy, with subsequent 8 mg doses every 8 hours after the first dose for each day radiotherapy is given.
Postoperative | 16 mg administered 1 hour before induction of anesthesia.

Table 2: Pediatric Recommended Dosage Regimen for Prevention of Nausea and Vomiting
Indication | Dosage Regimen
Moderately Emetogenic Cancer Chemotherapy | 12 to 17 years of age: 8 mg administered 30 minutes before the start of chemotherapy, with a subsequent 8 mg dose 4 and 8 hours after the first dose. Then administer 8 mg three times a day for 1 to 2 days after completion of chemotherapy. 4 to 11 years of age: 4 mg administered 30 minutes before the start of chemotherapy, with a subsequent 4 mg dose 4 and 8 hours after the first dose. Then administer 4 mg three times a day for 1 to 2 days after completion of chemotherapy.

2.2 Dosage in Hepatic Impairment

In patients with severe hepatic impairment (Child-Pugh score of 10 or greater), do not exceed a total daily dose of 8 mg [see Use in Specific Populations (8.6), Clinical Pharmacology (12.3)] .

3 DOSAGE FORMS AND STRENGTHS

Ondansetron tablets USP, 4 mg are white to off-white, oval shaped, film-coated tablets debossed with ‘F’ on one side and ‘91’ on the other side.
Ondansetron tablets USP, 8 mg are yellow colored, oval shaped, film-coated tablets debossed with ‘F’ on one side and ‘92’ on the other side.
Ondansetron tablets USP, 24 mg are pink colored, oval shaped, film-coated tablets debossed with ‘C’ on one side and ‘71’ on the other side.

4 CONTRAINDICATIONS

Ondansetron tablets are contraindicated in patients:

- known to have hypersensitivity (e.g., anaphylaxis) to ondansetron or any of the components of the formulation [see Adverse Reactions (6.2)] .
- receiving concomitant apomorphine due to the risk of profound hypotension and loss of consciousness.

5 WARNINGS AND PRECAUTIONS

5.1 Hypersensitivity Reactions

Hypersensitivity reactions, including anaphylaxis and bronchospasm, have been reported in patients who have exhibited hypersensitivity to other selective 5-HT3 receptor antagonists. If hypersensitivity reactions occur, discontinue use of ondansetron; treat promptly per standard of care and monitor until signs and symptoms resolve [see Contraindications (4)].

5.2 QT Prolongation

Electrocardiogram (ECG) changes including QT interval prolongation have been seen in patients receiving ondansetron. In addition, postmarketing cases of Torsade de Pointes have been reported in patients using ondansetron. Avoid ondansetron in patients with congenital long QT syndrome. ECG monitoring is recommended in patients with electrolyte abnormalities (e.g., hypokalemia or hypomagnesemia), congestive heart failure, bradyarrhythmias, or patients taking other medicinal products that lead to QT prolongation [see Clinical Pharmacology (12.2)] .

5.3 Serotonin Syndrome

The development of serotonin syndrome has been reported with 5-HT3 receptor antagonists alone. Most reports have been associated with concomitant use of serotonergic drugs (e.g., selective serotonin reuptake inhibitors (SSRIs), serotonin and norepinephrine reuptake inhibitors (SNRIs), monoamine oxidase inhibitors, mirtazapine, fentanyl, lithium, tramadol, and intravenous methylene blue). Some of the reported cases were fatal. Serotonin syndrome occurring with overdose of ondansetron alone has also been reported. The majority of reports of serotonin syndrome related to 5-HT3 receptor antagonist use occurred in a post-anesthesia care unit or an infusion center.
Symptoms associated with serotonin syndrome may include the following combination of signs and symptoms: mental status changes (e.g., agitation, hallucinations, delirium, and coma), autonomic instability (e.g., tachycardia, labile blood pressure, dizziness, diaphoresis, flushing, hyperthermia), neuromuscular symptoms (e.g., tremor, rigidity, myoclonus, hyperreflexia, incoordination), seizures, with or without gastrointestinal symptoms (e.g., nausea, vomiting, diarrhea). Patients should be monitored for the emergence of serotonin syndrome, especially with concomitant use of ondansetron and other serotonergic drugs. If symptoms of serotonin syndrome occur, discontinue ondansetron and initiate supportive treatment. Patients should be informed of the increased risk of serotonin syndrome, especially if ondansetron is used concomitantly with other serotonergic drugs [see Drug Interactions (7.1), Overdosage (10)] .

5.4 Masking of Progressive Ileus and Gastric Distension

The use of ondansetron in patients following abdominal surgery or in patients with chemotherapy-induced nausea and vomiting may mask a progressive ileus and/or gastric distension. Monitor for decreased bowel activity, particularly in patients with risk factors for gastrointestinal obstruction. Ondansetron is not a drug that stimulates gastric or intestinal peristalsis. It should not be used instead of nasogastric suction.

6 ADVERSE REACTIONS

6.1 Clinical Trials Experience

Because clinical trials are conducted under widely varying conditions, adverse reaction rates observed in the clinical trials of a drug cannot be directly compared with rates in the clinical trials of another drug and may not reflect the rates observed in practice.

The following adverse reactions have been reported in clinical trials of patients treated with ondansetron, the active ingredient of ondansetron tablets. A causal relationship to therapy with ondansetron was unclear in many cases.

Prevention of Chemotherapy-induced Nausea and Vomiting

The most common adverse reactions reported in greater than or equal to 4% of 300 adults receiving a single 24 mg dose of ondansetron orally in 2 trials for the prevention of nausea and vomiting associated with highly emetogenic chemotherapy (cisplatin greater than or equal to 50 mg/m^2) were: headache (11%) and diarrhea (4%).

The most common adverse reactions reported in 4 trials in adults for the prevention of nausea and vomiting associated with moderately emetogenic chemotherapy (primarily cyclophosphamide-based regimens) are shown in Table 3.

Table 3. Most Common Adverse Reactions in Adultsa for the Prevention of Nausea and Vomiting Associated with Moderately Emetogenic Chemotherapy [Primarily Cyclophosphamide-based Regimens]
Adverse Reaction | Ondansetron 8 mg Twice Daily (n = 242) | Placebo (n = 262)
Headache | 58 (24%) | 34 (13%)
Malaise/fatigue | 32 (13%) | 6 (2%)
Constipation | 22 (9%) | 1 (<1%)
Diarrhea | 15 (6%) | 10 (4%)
a Reported in greater than or equal to 5% of patients treated with ondansetron and at a rate that exceeded placebo.

Less Common Adverse Reactions
Central Nervous System: Extrapyramidal reactions (less than 1% of patients).
Hepatic: Aspartate transaminase (AST) and/or alanine transaminase (ALT) values exceeded twice the upper limit of normal in approximately 1% to 2% of 723 patients receiving ondansetron and cyclophosphamide-based chemotherapy in U.S. clinical trials. The increases were transient and did not appear to be related to dose or duration of therapy. On repeat exposure, similar transient elevations in transaminase values occurred in some courses, but symptomatic hepatic disease did not occur. The role of cancer chemotherapy in these biochemical changes is unclear.
Liver failure and death has been reported in cancer patients receiving concurrent medications, including potentially hepatotoxic cytotoxic chemotherapy and antibiotics. The etiology of the liver failure is unclear.
Integumentary: Rash (approximately 1% of patients).
Other (less than 2%): Anaphylaxis, bronchospasm, tachycardia, angina, hypokalemia, electrocardiographic alterations, vascular occlusive events, and grand mal seizures. Except for bronchospasm and anaphylaxis, the relationship to ondansetron is unclear.
Prevention of Radiation-induced Nausea and Vomiting
The most common adverse reactions (greater than or equal to 2%) reported in patients receiving ondansetron and concurrent radiotherapy were similar to those reported in patients receiving ondansetron and concurrent chemotherapy and were headache, constipation, and diarrhea.
Prevention of Postoperative Nausea and Vomiting
The most common adverse reactions reported in adults in trial(s) of prevention of postoperative nausea and vomiting are shown in Table 4. In these trial(s) patients were receiving multiple concomitant perioperative and postoperative medications in both treatment groups.

Table 4. Most Common Adverse Reactions in Adultsa for the Prevention of Postoperative Nausea and Vomiting
Adverse Reaction | Ondansetron 16 mg as a Single Dose (n = 550) | Placebo (n = 531)
Headache | 49 (9%) | 27 (5%)
Hypoxia | 49 (9%) | 35 (7%)
Pyrexia | 45 (8%) | 34 (6%)
Dizziness | 36 (7%) | 34 (6%)
Gynecological disorder | 36 (7%) | 33 (6%)
Anxiety/agitation | 33 (6%) | 29 (5%)
Urinary retention | 28 (5%) | 18 (3%)
Pruritus | 27 (5%) | 20 (4%)
a Reported in greater than or equal to 5% of patients treated with ondansetron and at a rate that exceeded placebo.

6.2 Postmarketing Experience

The following adverse reactions have been identified during post-approval use of ondansetron. Because these reactions are reported voluntarily from a population of uncertain size, it is not always possible to reliably estimate their frequency or establish a causal relationship to drug exposure.
Cardiovascular
Arrhythmias (including ventricular and supraventricular tachycardia, premature ventricular contractions, and atrial fibrillation), bradycardia, electrocardiographic alterations (including second-degree heart block, QT/QTc interval prolongation, and ST segment depression), palpitations, and syncope. Rarely and predominantly with intravenous ondansetron, transient ECG changes including QT interval prolongation have been reported.
General
Flushing. Rare cases of hypersensitivity reactions, sometimes severe (e.g., anaphylactic reactions, angioedema, bronchospasm, shortness of breath, hypotension, laryngeal edema, stridor) have also been reported.
Laryngospasm, shock, and cardiopulmonary arrest have occurred during allergic reactions in patients receiving injectable ondansetron.
Hepatobiliary
Liver enzyme abnormalities.
Lower Respiratory
Hiccups.
Neurology
Oculogyric crisis, appearing alone, as well as with other dystonic reactions.
Skin
Urticaria, Stevens-Johnson syndrome, and toxic epidermal necrolysis.
Eye Disorders
Cases of transient blindness, predominantly during intravenous administration, have been reported. These cases of transient blindness were reported to resolve within a few minutes up to 48 hours.

7 DRUG INTERACTIONS

7.1 Serotonergic Drugs

Serotonin syndrome (including altered mental status, autonomic instability, and neuromuscular symptoms) has been described following the concomitant use of 5-HT3 receptor antagonists and other serotonergic drugs, including selective serotonin reuptake inhibitors (SSRIs) and serotonin and noradrenaline reuptake inhibitors (SNRIs). Monitor for the emergence of serotonin syndrome. If symptoms occur, discontinue ondansetron and initiate supportive treatment [see Warnings and Precautions (5.3)] .

7.2 Drugs Affecting Cytochrome P-450 Enzymes

Ondansetron does not itself appear to induce or inhibit the cytochrome P-450 drug-metabolizing enzyme system of the liver [see Clinical Pharmacology (12.3)] . Because ondansetron is metabolized by hepatic cytochrome P-450 drug-metabolizing enzymes (CYP3A4, CYP2D6, CYP1A2), inducers or inhibitors of these enzymes may change the clearance and, hence, the half-life of ondansetron. In patients treated with potent inducers of CYP3A4 (i.e., phenytoin, carbamazepine, and rifampin), the clearance of ondansetron was significantly increased and ondansetron blood concentrations were decreased. However, on the basis of available data, no dosage adjustment for ondansetron is recommended for patients on these drugs [see Clinical Pharmacology (12.3)] .

7.3 Tramadol

Although no pharmacokinetic drug interaction between ondansetron and tramadol has been observed, data from 2 small trials indicate that when used together, ondansetron may increase patient-controlled administration of tramadol. Monitor patients to ensure adequate pain control when ondansetron is administered with tramadol.

7.4 Chemotherapy

Carmustine, etoposide, and cisplatin do not affect the pharmacokinetics of ondansetron.
In a crossover trial in 76 pediatric patients, intravenous ondansetron did not increase systemic concentrations of high-dose methotrexate.

7.5 Alfentanil and Atracurium

Ondansetron does not alter the respiratory depressant effects produced by alfentanil or the degree of neuromuscular blockade produced by atracurium. Interactions with general or local anesthetics have not been studied.

8 USE IN SPECIFIC POPULATIONS

8.1 Pregnancy

Risk Summary
Available data do not reliably inform the association of ondansetron and adverse fetal outcomes. Published epidemiological studies on the association between ondansetron and fetal outcomes have reported inconsistent findings and have important methodological limitations hindering interpretation [see Data]. Reproductive studies in rats and rabbits did not show evidence of harm to the fetus when ondansetron was administered during organogenesis at approximately 6 and 24 times the maximum recommended human oral dose of 24 mg/day, based on body surface area, respectively [see Data].
The background risk of major birth defects and miscarriage for the indicated population is unknown. In the U.S. general population, the estimated background risk of major birth defects and miscarriages in clinically recognized pregnancies is 2% to 4% and 15% to 20%, respectively.
Data
Human Data
Methodological limitations of the epidemiology studies preclude a reliable evaluation of the potential risk of adverse fetal outcomes with the use of ondansetron in pregnancy.
Two large retrospective cohort studies of ondansetron use in pregnancy have been published. In one study with 1,349 infants born to women who reported the use of ondansetron or received an ondansetron prescription in the first trimester, no increased risk for major congenital malformations was seen in aggregate analysis. In this same study, however, a sub-analysis for specific malformations reported an association between ondansetron exposure and cardiovascular defect (odds ratio (OR) 1.62 [95% CI (1.04, 2.14)]) and cardiac septal defect (OR 2.05 [95% CI (1.19, 3.28)]). The second study examined 1970 women who received ondansetron prescription during pregnancy and reported no association between ondansetron exposure and major congenital malformations, miscarriage or stillbirth, and infants of low birth weight or small for gestational age. Important methodological limitations with these studies include the uncertainty of whether women who filled a prescription actually took the medication, the concomitant use of other medications or treatments, and other unadjusted confounders that may account for the study findings.
A case-control study evaluating associations between several common non-cardiac malformations and multiple antiemetic drugs reported an association between maternal use of ondansetron and isolated cleft palate (reported adjusted OR = 2.37 [95% CI (1.18, 4.76)]). However, this association could be a chance finding, given the large number of drugs-birth defect comparisons in this study. It is unknown whether ondansetron exposure in utero in the cases of cleft palate occurred during the time of palate formation (the palate is formed between the 6th and 9th weeks of pregnancy) or whether mothers of infants with cleft palate used other medications or had other risk factors for cleft palate in the offspring. In addition, no cases of isolated cleft palate were identified in the aforementioned two large retrospective cohort studies. At this time, there is no clear evidence that ondansetron exposure in early pregnancy can cause cleft palate.
Animal Data
In embryo-fetal development studies in rats and rabbits, pregnant animals received oral doses of ondansetron up to 15 mg/kg/day and 30 mg/kg/day, respectively, during the period of organogenesis. With the exception of a slight decrease in maternal body weight gain in the rabbits, there were no significant effects of ondansetron on the maternal animals or the development of the offspring. At doses of 15 mg/kg/day in rats and 30 mg/kg/day in rabbits, the maternal exposure margin was approximately 6 and 24 times the maximum recommended human oral dose of 24 mg/day, respectively, based on body surface area.
In a pre- and postnatal developmental toxicity study, pregnant rats received oral doses of ondansetron up to 15 mg/kg/day from Day 17 of pregnancy to litter Day 21. With the exception of a slight reduction in maternal body weight gain, there were no effects upon the pregnant rats and the pre- and postnatal development of their offspring, including reproductive performance of the mated F1 generation. At a dose of 15 mg/kg/day in rats, the maternal exposure margin was approximately 6 times the maximum recommended human oral dose of 24 mg/day, based on body surface area.

8.2 Lactation

Risk Summary
It is not known whether ondansetron is present in human milk. There are no data on the effects of ondansetron on the breastfed infant or the effects on milk production. However, it has been demonstrated that ondansetron is present in the milk of rats.
The developmental and health benefits of breastfeeding should be considered along with the mother’s clinical need for ondansetron and any potential adverse effects on the breast-fed infant from ondansetron or from the underlying maternal condition.

8.4 Pediatric Use

The safety and effectiveness of orally administered ondansetron have been established in pediatric patients 4 years and older for the prevention of nausea and vomiting associated with moderately emetogenic cancer chemotherapy. Use of ondansetron in these age-groups is supported by evidence from adequate and well- controlled studies of ondansetron in adults with additional data from 3 open-label, uncontrolled, non-US trials in 182 pediatric patients aged 4 to 18 years with cancer who were given a variety of cisplatin or noncisplatin regimens [see Dosage and Administration (2.2), Clinical Studies (14.1)] .
Additional information on the use of ondansetron in pediatric patients may be found in Ondansetron Injection prescribing information.
The safety and effectiveness of orally administered ondansetron have not been established in pediatric patients for:

- prevention of nausea and vomiting associated with highly emetogenic cancer chemotherapy.
- prevention of nausea and vomiting associated with radiotherapy.
- prevention of postoperative nausea and/or vomiting.

8.5 Geriatric Use

Of the total number of subjects enrolled in cancer chemotherapy-induced and postoperative nausea and vomiting in U.S.- and foreign-controlled clinical trials, for which there were subgroup analyses, 938 (19%) were aged 65 years and older.
No overall differences in safety or effectiveness were observed between subjects 65 years of age and older and younger subjects. A reduction in clearance and increase in elimination half-life were seen in patients older than 75 years compared with younger subjects [see Clinical Pharmacology (12.3)] . There were an insufficient number of patients older than 75 years of age and older in the clinical trials to permit safety or efficacy conclusions in this age-group. Other reported clinical experience has not identified differences in responses between the elderly and younger patients, but greater sensitivity of some older individuals cannot be ruled out. No dosage adjustment is needed in elderly patients.

8.6 Hepatic Impairment

No dosage adjustment is needed in patients with mild or moderate hepatic impairment.
In patients with severe hepatic impairment, clearance is reduced and the apparent volume of distribution is increased, resulting in a significant increase in the half-life of ondansetron. Therefore, do not exceed a total daily dose of 8 mg in patients with severe hepatic impairment (Child-Pugh score of 10 or greater) [see Dosage and Administration (2.2), Clinical Pharmacology (12.3)] .

8.7 Renal Impairment

No dosage adjustment is recommended for patients with any degree of renal impairment (mild, moderate, or severe). There is no experience beyond first-day administration of ondansetron [see Clinical Pharmacology (12.3)] .

9 DRUG ABUSE AND DEPENDENCE

Animal studies have shown that ondansetron is not discriminated as a benzodiazepine nor does it substitute for benzodiazepines in direct addiction studies.

10 OVERDOSAGE

There is no specific antidote for ondansetron overdose. Patients should be managed with appropriate supportive therapy.
In addition to the adverse reactions listed above, the following adverse reactions have been described in the setting of ondansetron overdose: “Sudden blindness” (amaurosis) of 2 to 3 minutes’ duration plus severe constipation occurred in one patient that was administered 72 mg of ondansetron intravenously as a single dose. Hypotension (and faintness) occurred in a patient that took 48 mg of ondansetron tablets. Following infusion of 32 mg over only a 4-minute period, a vasovagal episode with transient second-degree heart block was observed. In all instances, the adverse reactions resolved completely.
Pediatric cases consistent with serotonin syndrome have been reported after inadvertent oral overdoses of ondansetron (exceeding estimated ingestion of 5 mg per kg) in young children. Reported symptoms included somnolence, agitation, tachycardia, tachypnea, hypertension, flushing, mydriasis, diaphoresis, myoclonic movements, horizontal nystagmus, hyperreflexia, and seizure. Patients required supportive care, including intubation in some cases, with complete recovery without sequelae within 1 to 2 days.

11 DESCRIPTION

The active ingredient in ondansetron tablets, USP is ondansetron hydrochloride as the dihydrate, the racemic form of ondansetron and a selective blocking agent of the serotonin 5-HT3 receptor type. Chemically it is (±) 1, 2, 3, 9-tetrahydro-9-methyl-3-[(2-methyl-1H-imidazol-1-yl)methyl]-4H-carbazol-4-one, monohydrochloride, dihydrate. It has the following structural formula:
The molecular formula is C18H19N3O•HCl•2H2O, representing a molecular weight of 365.9.
Ondansetron hydrochloride USP (dihydrate) is a white to off-white powder that is soluble in water and normal saline.
Ondansetron tablets, USP for oral administration contain ondansetron hydrochloride USP (dihydrate) equivalent to 4 mg or 8 mg or 24 mg of ondansetron. Each film-coated tablet also contains the inactive ingredients anhydrous lactose, microcrystalline cellulose, pregelatinized starch (maize), magnesium stearate, triacetin, titanium dioxide and hypromellose. In addition 8 mg tablet also contains iron oxide yellow and 24 mg tablet also contains iron oxide red.

Meets USP dissolution test 6.

12 CLINICAL PHARMACOLOGY

12.1 Mechanism of Action

Ondansetron is a selective 5-HT3 receptor antagonist. While its mechanism of action has not been fully characterized, ondansetron is not a dopamine-receptor antagonist. Serotonin receptors of the 5-HT3 type are present both peripherally on vagal nerve terminals and centrally in the chemoreceptor trigger zone of the area postrema. It is not certain whether ondansetron’s antiemetic action is mediated centrally, peripherally, or in both sites. However, cytotoxic chemotherapy appears to be associated with release of serotonin from the enterochromaffin cells of the small intestine. In humans, urinary 5-hydroxyindoleacetic acid (5-HIAA) excretion increases after cisplatin administration in parallel with the onset of emesis. The released serotonin may stimulate the vagal afferents through the 5-HT3 receptors and initiate the vomiting reflex.

12.2 Pharmacodynamics

In healthy subjects, single intravenous doses of 0.15 mg/kg of ondansetron had no effect on esophageal motility, gastric motility, lower esophageal sphincter pressure, or small intestinal transit time. Multiday administration of ondansetron has been shown to slow colonic transit in healthy subjects. Ondansetron has no effect on plasma prolactin concentrations.
Cardiac Electrophysiology
QTc interval prolongation was studied in a double-blind, single intravenous dose, placebo- and positive- controlled, crossover trial in 58 healthy subjects. The maximum mean (95% upper confidence bound) difference in QTcF from placebo after baseline correction was 19.5 (21.8) milliseconds and 5.6 (7.4) milliseconds after 15 minute intravenous infusions of 32 mg and 8 mg of ondansetron injection, respectively. A significant exposure- response relationship was identified between ondansetron concentration and ΔΔQTcF. Using the established exposure-response relationship, 24 mg infused intravenously over 15 minutes had a mean predicted (95% upper prediction interval) ΔΔQTcF of 14.0 (16.3) milliseconds. In contrast, 16 mg infused intravenously over 15 minutes using the same model had a mean predicted (95% upper prediction interval) ΔΔQTcF of 9.1 (11.2) milliseconds. In this study, the 8 mg dose infused over 15 minutes did not prolong the QT interval to any clinically relevant extent.

12.3 Pharmacokinetics

Absorption
Ondansetron is absorbed from the gastrointestinal tract and undergoes some first-pass metabolism. Mean bioavailability in healthy subjects, following administration of a single 8 mg tablet, is approximately 56%.
Ondansetron systemic exposure does not increase proportionately to dose. The AUC from a 16 mg tablet was 24% greater than predicted from an 8 mg tablet dose. This may reflect some reduction of first-pass metabolism at higher oral doses.
Food Effects: Bioavailability is also slightly enhanced by the presence of food.
Distribution
Plasma protein binding of ondansetron as measured in vitro was 70% to 76% over the concentration range of 10 to 500 ng/mL. Circulating drug also distributes into erythrocytes.
Elimination
Metabolism and Excretion: Ondansetron is extensively metabolized in humans, with approximately 5% of a radiolabeled dose recovered as the parent compound from the urine. The metabolites are observed in the urine. The primary metabolic pathway is hydroxylation on the indole ring followed by subsequent glucuronide or sulfate conjugation.
In vitro metabolism studies have shown that ondansetron is a substrate for human hepatic cytochrome P-450 enzymes, including CYP1A2, CYP2D6, and CYP3A4. In terms of overall ondansetron turnover, CYP3A4 played the predominant role. Because of the multiplicity of metabolic enzymes capable of metabolizing ondansetron, it is likely that inhibition or loss of one enzyme (e.g., CYP2D6 genetic deficiency) will be compensated by others and may result in little change in overall rates of ondansetron elimination.
Although some nonconjugated metabolites have pharmacologic activity, these are not found in plasma at concentrations likely to significantly contribute to the biological activity of ondansetron.
Specific Populations
Age: Geriatric Population: A reduction in clearance and increase in elimination half-life are seen in patients older than 75 years compared to younger subjects [see Use in Specific Populations (8.5)] .
Sex: Gender differences were shown in the disposition of ondansetron given as a single dose. The extent and rate of absorption are greater in women than men. Slower clearance in women, a smaller apparent volume of distribution (adjusted for weight), and higher absolute bioavailability resulted in higher plasma ondansetron concentrations. These higher plasma concentrations may in part be explained by differences in body weight between men and women. It is not known whether these sex-related differences were clinically important. More detailed pharmacokinetic information is contained in Tables 5 and 6.

Table 5. Pharmacokinetics in Male and Female Healthy Subjects after a Single Dose of a Ondansetron 8 mg Tablet
Age-group (years) Sex (M/F) | Mean Weight (kg) | N | Peak Plasma Concentration (ng/mL) | Time of Peak Plasma Concentration (h) | Mean Elimination Half-life (h) | Systemic Plasma Clearance L/h/kg | Absolute Bioavailability
18 to 40 M F | 69.0 62.7 | 6 5 | 26.2 42.7 | 2.0 1.7 | 3.1 3.5 | 0.403 0.354 | 0.483 0.663
61 to 74 M F | 77.5 60.2 | 6 6 | 24.1 52.4 | 2.1 1.9 | 4.1 4.9 | 0.384 0.255 | 0.585 0.643
≥75 M F | 78.0 67.6 | 5 6 | 37.0 46.1 | 2.2 2.1 | 4.5 6.2 | 0.277 0.249 | 0.619 0.747

Table 6. Pharmacokinetics in Male and Female Healthy Subjects after a Single Dose of a Ondansetron 24 mg Tablet
Age-group (years) Sex (M/F) | Mean Weight (kg) | N | Peak Plasma Concentration (ng/mL) | Time of Peak Plasma Concentration (h) | Mean Elimination Half-life (h)
18 to 43 M F | 84.1 71.8 | 8 8 | 125.8 194.4 | 1.9 1.6 | 4.7 5.8

Renal Impairment: Renal impairment is not expected to significantly influence the total clearance of ondansetron as renal clearance represents only 5% of the overall clearance. However, the mean plasma clearance of ondansetron was reduced by about 50% in patients with severe renal impairment (creatinine clearance less than 30 mL/min). The reduction in clearance was variable and not consistent with an increase in half-life [see Use in Specific Populations (8.7)] .
Hepatic Impairment: In patients with mild-to-moderate hepatic impairment, clearance is reduced 2-fold and mean half-life is increased to 11.6 hours compared with 5.7 hours in healthy subjects. In patients with severe hepatic impairment (Child-Pugh score of 10 or greater), clearance is reduced 2-fold to 3-fold and apparent volume of distribution is increased with a resultant increase in half-life to 20 hours [see Dosage and Administration (2.2), Use in Specific Populations (8.6)] .
Drug Interaction Studies
CYP 3A4 Inducers: Ondansetron elimination may be affected by cytochrome P-450 inducers. In a pharmacokinetic trial of 16 epileptic patients maintained chronically on CYP3A4 inducers, carbamazepine, or phenytoin, a reduction in AUC, Cmax, and t½ of ondansetron was observed. This resulted in a significant increase in the clearance of ondansetron. However, this increase is not thought to be clinically relevant [see Drug Interactions (7.2)] .
Chemotherapeutic Agents: Carmustine, etoposide, and cisplatin do not affect the pharmacokinetics of ondansetron [see Drug Interactions (7.4)] .
Antacids: Concomitant administration of antacids does not alter the absorption of ondansetron.

13 NONCLINICAL TOXICOLOGY

13.1 Carcinogenesis, Mutagenesis, Impairment of Fertility

Carcinogenic effects were not seen in 2-year studies in rats and mice with oral ondansetron doses up to 10 mg/kg per day and 30 mg/kg per day, respectively (approximately 4 and 6 times the maximum recommended human oral dose of 24 mg per day, based on body surface area).
Ondansetron was not mutagenic in standard tests for mutagenicity.
Oral administration of ondansetron up to 15 mg/kg per day (approximately 6 times the maximum recommended human oral dose of 24 mg per day, based on body surface area) did not affect fertility or general reproductive performance of male and female rats.

14 CLINICAL STUDIES

14.1 Prevention of Chemotherapy-induced Nausea and Vomiting

Highly Emetogenic Chemotherapy
In two randomized, double-blind, monotherapy trials, a single 24 mg oral dose of ondansetron was superior to a relevant historical placebo control in the prevention of nausea and vomiting associated with highly emetogenic cancer chemotherapy, including cisplatin greater than or equal to 50 mg/m^2. Steroid administration was excluded from these clinical trials. More than 90% of patients receiving a cisplatin dose greater than or equal to 50 mg/m^2 in the historical placebo comparator experienced vomiting in the absence of antiemetic therapy.
The first trial compared oral doses of ondansetron 24 mg as a single dose, 8 mg every 8 hours for 2 doses, and 32 mg as a single dose in 357 adult cancer patients receiving chemotherapy regimens containing cisplatin greater than or equal to 50 mg/m^2. The first or single dose was administered 30 minutes prior to chemotherapy. A total of 66% of patients in the ondansetron 24 mg once-a-day group, 55% in the ondansetron 8 mg twice-a-day group, and 55% in the ondansetron 32 mg once-a-day group completed the 24-hour trial period with 0 emetic episodes and no rescue antiemetic medications, the primary endpoint of efficacy. Each of the 3 treatment groups was shown to be statistically significantly superior to a historical placebo control.
In the same trial, 56% of patients receiving a single 24 mg oral dose of ondansetron experienced no nausea during the 24-hour trial period, compared with 36% of patients in the oral ondansetron 8 mg twice-a-day group (P = 0.001) and 50% in the oral ondansetron 32 mg once-a-day group. Dosage regimens of ondansetron 8 mg twice daily and 32 mg once daily are not recommended for the prevention of nausea and vomiting associated with highly emetogenic chemotherapy [see Dosage and Administration (2.1)] .
In a second trial, efficacy of a single 24 mg oral dose of ondansetron for the prevention of nausea and vomiting associated with highly emetogenic cancer chemotherapy, including cisplatin greater than or equal to 50 mg/m^2, was confirmed.
Moderately Emetogenic Chemotherapy
A randomized, placebo-controlled, double-blind trial was conducted in the U.S. in 67 patients receiving a cyclophosphamide-based chemotherapy regimen containing doxorubicin. The first 8 mg dose of ondansetron was administered 30 minutes before the start of chemotherapy, with a subsequent dose 8 hours after the first dose, followed by 8 mg of ondansetron twice a day for 2 days after the completion of chemotherapy.
Ondansetron was significantly more effective than placebo in preventing vomiting. Treatment response was based on the total number of emetic episodes over the 3-day trial period. The results of this trial are summarized in Table 7:

Table 7. Emetic Episodes: Treatment Response in Patients Receiving Moderately Emetogenic Chemotherapy (Cyclophosphamide-based Regimen Containing Doxorubicin)
 | Ondansetron (n = 33) | Placebo (n = 34) | P Value
Treatment response 0 Emetic episodes 1 to 2 Emetic episodes More than 2 emetic episodes/withdrawn | 20 (61%) 6 (18%) 7 (21%) | 2 (6%) 8 (24%) 24 (71%) | <0.001 <0.001
Median number of emetic episodes | 0.0 | Undefineda
Median time to first emetic episode (hours) | Undefinedb | 6.5
a Median undefined since at least 50% of the patients were withdrawn or had more than 2 emetic episodes.
b Median undefined since at least 50% of patients did not have any emetic episodes.

In a double-blind U.S. trial in 336 patients receiving a cyclophosphamide-based chemotherapy regimen containing either methotrexate or doxorubicin, ondansetron 8 mg administered twice a day was as effective as ondansetron 8 mg administered 3 times a day in preventing nausea and vomiting. Ondansetron 8 mg three times daily is not a recommended regimen for the treatment of moderately emetogenic chemotherapy [see Dosage and Administration (2.1)] .
Treatment response was based on the total number of emetic episodes over the 3-day trial period. See Table 8 for the details of the dosage regimens studied and results of this trial.

Table 8. Emetic Episodes: Treatment Response after Ondansetron Tablets Administered Twice a Day and Three Times a Day
 | Ondansetron Tablets
 | 8 mg Twice Dailya (n = 165) | 8 mg Three Times a Dayb (n = 171)
Treatment response 0 Emetic episodes 1to 2 Emetic episodes More than 2 emetic episodes/withdrawn | 101 (61%) 16 (10%) 48 (29%) | 99 (58%) 17 (10%) 55 (32%)
Median number of emetic episodes | 0.0 | 0.0
Median time to first emetic episode (h) | Undefinedc | Undefinedc
Median nausea scores (0 to 100)d | 6 | 6
a The first 8 mg dose was administered 30 minutes before the start of emetogenic chemotherapy, with a subsequent 8 mg dose 8 hours after the first dose, followed by 8 mg administered twice a day for 2 days after the completion of chemotherapy.
b The first 8 mg dose was administered 30 minutes before the start of emetogenic chemotherapy, with subsequent 8 mg doses at 4 hours and 8 hours after the first dose, followed by 8 mg administered 3 times a day for 2 days after the completion of chemotherapy.
c Median undefined since at least 50% of patients did not have any emetic episodes.
d Visual analog scale assessment: 0 = no nausea, 100 = nausea as bad as it can be.

Re-treatment
In single-arm trials, 148 patients receiving cyclophosphamide-based chemotherapy were re-treated with ondansetron 8 mg three times daily during subsequent chemotherapy for a total of 396 re-treatment courses. No emetic episodes occurred in 314 (79%) of the re-treatment courses, and only 1 to 2 emetic episodes occurred in 43 (11%) of the re-treatment courses.
Pediatric Trials
Three open-label, single-arm, non-U.S. trials have been performed with 182 pediatric patients aged 4 to 18 years with cancer who were given a variety of cisplatin or noncisplatin regimens. The initial dose of ondansetron injection ranged from 0.04 to 0.87 mg per kg (total dose of 2.16 mg to 12 mg) followed by the administration of oral doses of ondansetron ranging from 4 to 24 mg daily for 3 days. In these trials, 58% of the 170 evaluable patients had a complete response (no emetic episodes) on Day 1. In two trials the response rates to ondansetron 4 mg three times a day in patients younger than 12 years was similar to ondansetron 8 mg three times daily in patients 12 to 18 years. Prevention of emesis in these pediatric patients was essentially the same as for adults.

14.2 Radiation-induced Nausea and Vomiting

Total Body Irradiation
In a randomized, placebo-controlled, double-blind trial in 20 patients, 8 mg of ondansetron administered 1.5 hours before each fraction of radiotherapy for 4 days was significantly more effective than placebo in preventing vomiting induced by total body irradiation. Total body irradiation consisted of 11 fractions (120 cGy per fraction) over 4 days for a total of 1,320 cGy. Patients received 3 fractions for 3 days, then 2 fractions on Day 4.
Single High-dose Fraction Radiotherapy
In an active-controlled, double-blind trial in 105 patients receiving single high-dose radiotherapy (800 to 1,000 cGy) over an anterior or posterior field size of greater than or equal to 80 cm^2 to the abdomen, ondansetron was significantly more effective than metoclopramide with respect to complete control of emesis (0 emetic episodes). Patients received the first dose of ondansetron (8 mg) or metoclopramide (10 mg) 1 to 2 hours before radiotherapy. If radiotherapy was given in the morning, 8 mg of ondansetron or 10 mg of metoclopramide was administered in the late afternoon and repeated again before bedtime. If radiotherapy was given in the afternoon, patients took 8 mg of ondansetron or 10 mg of metoclopramide only once before bedtime. Patients continued the doses of oral medication three times daily for 3 days.
Daily Fractionated Radiotherapy
In an active-controlled, double-blind trial in 135 patients receiving a 1- to 4-week course of fractionated radiotherapy (180 cGy doses) over a field size of greater than or equal to 100 cm^2 to the abdomen, ondansetron was significantly more effective than prochlorperazine with respect to complete control of emesis (0 emetic episodes). Patients received the first dose of ondansetron (8 mg) or prochlorperazine (10 mg) 1 to 2 hours before the first daily radiotherapy fraction, with subsequent 8 mg doses approximately every 8 hours on each day of radiotherapy.

14.3 Postoperative Nausea and Vomiting

In two placebo-controlled, double-blind trials (one conducted in the U.S. and the other outside the U.S.) in 865 females undergoing inpatient surgical procedures, ondansetron 16 mg as a single dose or placebo was administered one hour before the induction of general balanced anesthesia (barbiturate, opioid, nitrous oxide, neuromuscular blockade, and supplemental isoflurane or enflurane), ondansetron tablets was significantly more effective than placebo in preventing postoperative nausea and vomiting.
No trials have been performed in males.

16 HOW SUPPLIED/STORAGE AND HANDLING

Ondansetron Tablets USP, 4 mg are white to off-white, oval shaped, film-coated tablets debossed with ‘F’ on one side and ‘91’ on the other side.
NDC

60760-636-10 BOTTLES OF 10

60760-636-16 BOTTLES OF 16

60760-636-20 BOTTLES OF 20

60760-636-30 BOTTLES OF 30 - INACTIVE

Store at 20° to 25°C (68° to 77°F); excursions permitted to 15° to 30°C (59° to 86°F) [see USP Controlled Room Temperature]. Protect from light.

17 PATIENT COUNSELING INFORMATION

QT Prolongation
Inform patients that ondansetron tablets may cause serious cardiac arrhythmias such as QT prolongation. Instruct patients to tell their healthcare provider right away if they perceive a change in their heart rate, if they feel lightheaded, or if they have a syncopal episode.
Hypersensitivity Reactions
Inform patients that ondansetron tablets may cause hypersensitivity reactions, some as severe as anaphylaxis and bronchospasm. Instruct patients to immediately report any signs and symptoms of hypersensitivity reactions, including fever, chills, rash, or breathing problems to their healthcare provider.
Masking of Progressive Ileus and Gastric Distension
Inform patients following abdominal surgery or those with chemotherapy-induced nausea and vomiting that ondansetron tablets may mask signs and symptoms of bowel obstruction. Instruct patients to immediately report any signs or symptoms consistent with a potential bowel obstruction to their healthcare provider.
Drug Interactions

- Instruct the patient to report the use of all medications, especially apomorphine, to their healthcare provider. Concomitant use of apomorphine and ondansetron may cause a significant drop in blood pressure and loss of consciousness.
- Advise patients of the possibility of serotonin syndrome with concomitant use of ondansetron and another serotonergic agent such as medications to treat depression and migraines. Advise patients to seek immediate medical attention if the following symptoms occur: changes in mental status, autonomic instability, neuromuscular symptoms with or without gastrointestinal symptoms.

Manufactured for:
Aurobindo Pharma USA, Inc.
2400 Route 130 North
Dayton, NJ 08810
Manufactured by:
Aurobindo Pharma Limited
Hyderabad–500 090, India
Revised: 11/2016